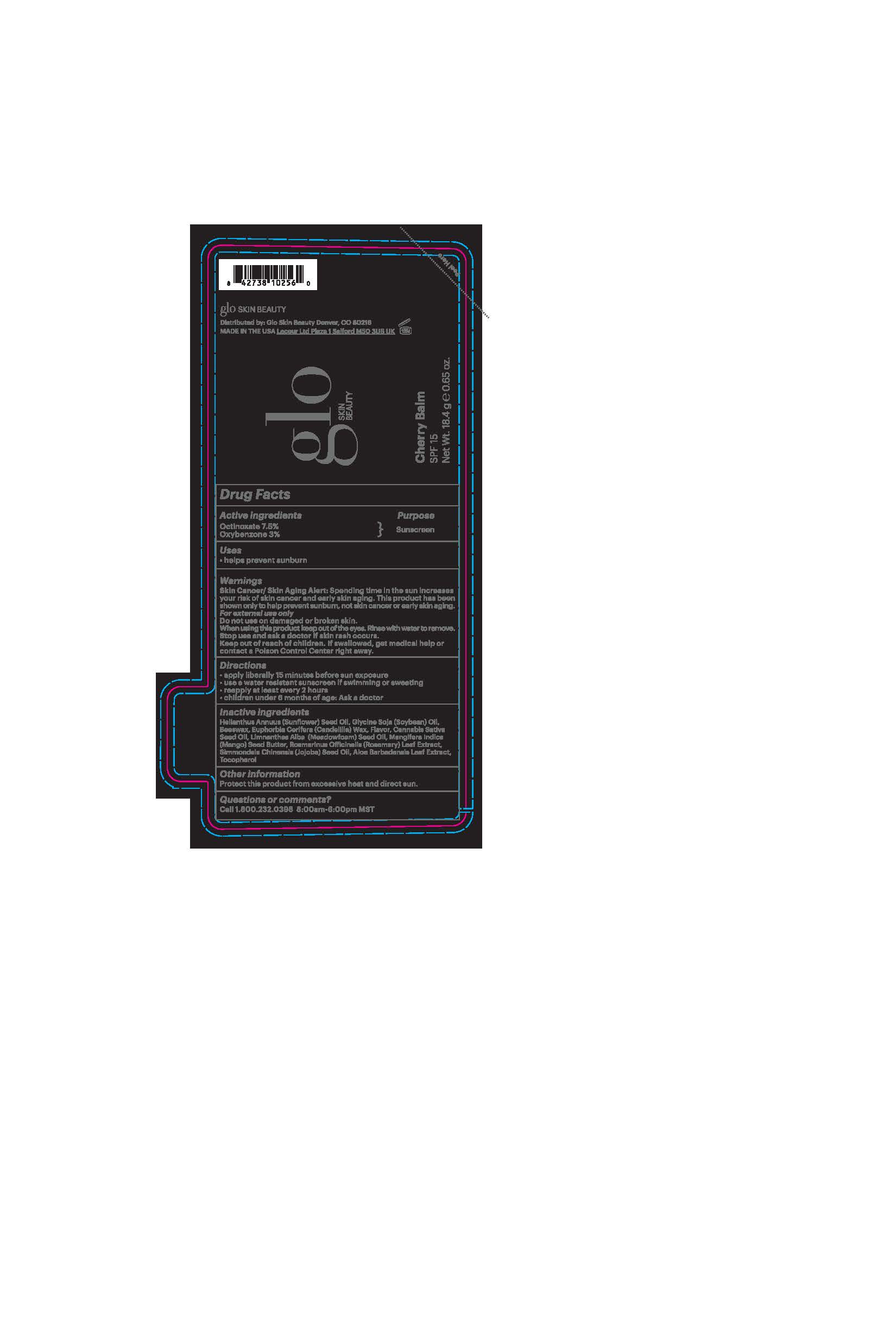 DRUG LABEL: glo SKIN BEAUTY Cherry Mint SPF 15
NDC: 60541-1600 | Form: STICK
Manufacturer: Hayden Caleel LLC
Category: otc | Type: HUMAN OTC DRUG LABEL
Date: 20171227

ACTIVE INGREDIENTS: OCTINOXATE 7.5 g/1 g; OXYBENZONE 3 g/1 g
INACTIVE INGREDIENTS: HELIANTHUS ANNUUS SEED WAX; SOYBEAN OIL; CANDELILLA WAX; CANNABIS SATIVA SEED OIL; LIMNANTHES ALBA WHOLE; MANGIFERA INDICA SEED BUTTER; MENTHA PIPERITA; ROSMARINUS OFFICINALIS WHOLE; SIMMONDSIA CHINENSIS SEED; ALOE VERA LEAF; TOCOPHEROL

DRUG FACTS

Active Ingredients

Octinoxate 7.5%
Oxybenzone 3%

Uses

• helps prevent sunburn

Warnings

Skin Cancer/Skin Agining Alert: Spending time in the sun increases your skin cancer and early skin aging. This product has been shown only to prevent sunberun, not skin cancer or early skin aging.

For external use only
Do not use on damaged or broken skin
When using this product keep out of eyes. Rinse with water to remove.
Stop use and ask a docor if rash occurs
Keep out of reach of children. If swalled, get medical help or contact a Poison Control Center right away.

Directions

• apply generously 15 minutes before sun exposure
• reapply at least every 2 hours
• use a water-resistant sunscreen if swimming or sweating
• children under 6 months of age: Ask a doctor

Inactive ingredients

Helianthus Annuus (Sunflower) Seed Oil, Glycine Soja (Soybean) Oil, Beeswax, Euphorbia Cerifera (Candalila) Wax, Cannabis Sativa Seed Oil, Limnanthes Alba (Meadowfoam) Seed Oil, Mangifera Indica (Mango) Seed Butter, Mentha Piperita (Peppermint) Oil, Rosmarinus Officinalis (Rosemary) Leaf Extract, Simmondsia Chinensis (Jojoba) Seed Oil, Aloe Barbaensis Leaf Extract, Tocopherol

Other Information

• protect the product in this container from excessive
heat and direct sun